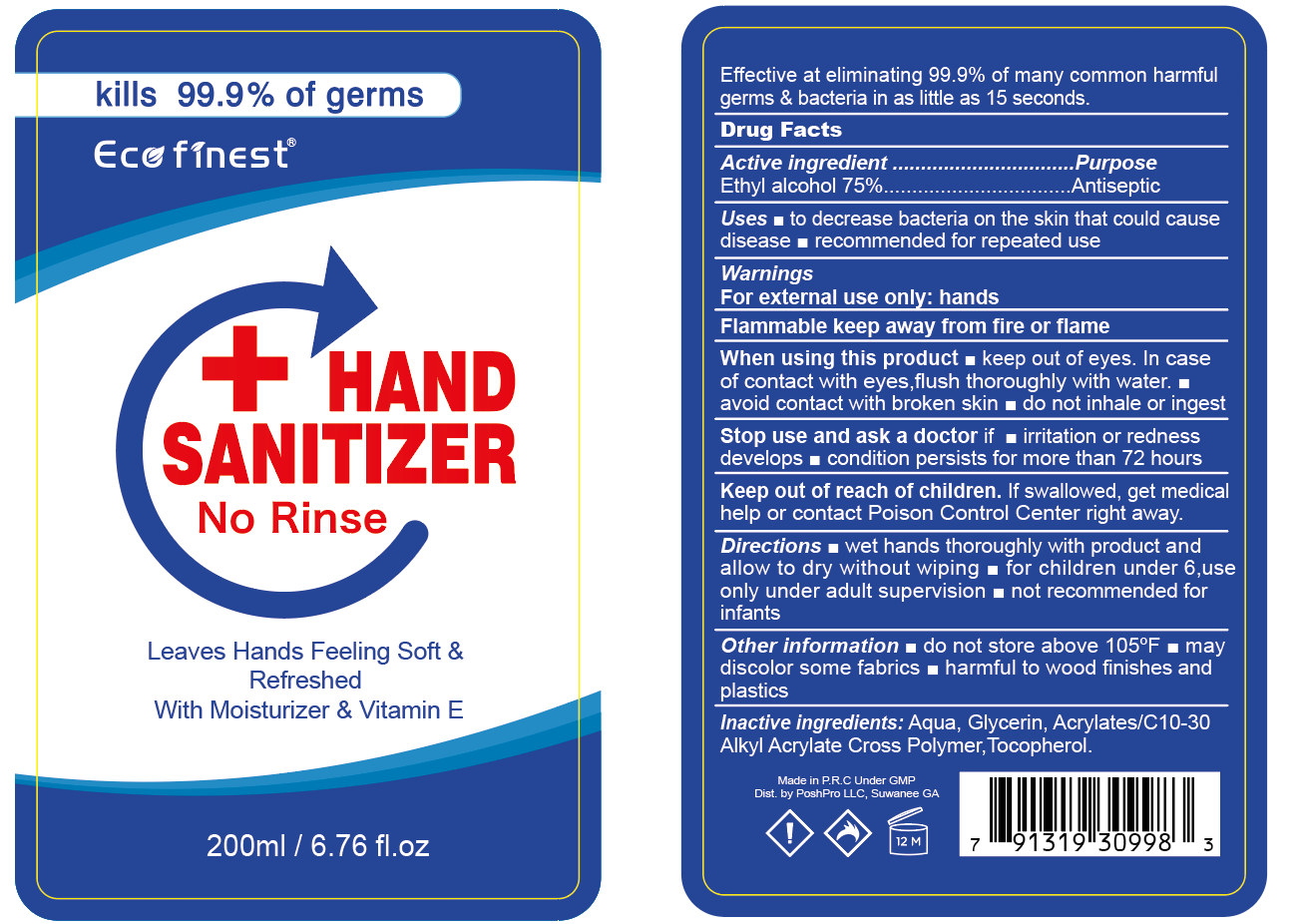 DRUG LABEL: Hand Sanitizer
NDC: 54237-018 | Form: GEL
Manufacturer: Guangzhou Daieme Cosmetic Co,.Ltd
Category: otc | Type: HUMAN OTC DRUG LABEL
Date: 20200731

ACTIVE INGREDIENTS: ALCOHOL 150 mL/200 mL
INACTIVE INGREDIENTS: CARBOMER INTERPOLYMER TYPE A (55000 CPS); GLYCERIN; TOCOPHEROL; WATER

DOSAGE AND ADMINISTRATION

store between 15-30°C (59 86°F),avoid freezing and excessive heat above 40°C (104°F)

INACTIVE INGREDIENT

Aqua, Glycerin, Acrylates/C10-30 Alkyl Acrylate Cross Polymer, Tocopherol

INDICATIONS AND USAGE

wet hands thoroughly with product and allow to dry without wiping

ACTIVE INGREDIENT

Alcohol

keep out of reach of children

PURPOSE

Disinfection
Sterilization
No Rinseing

WARNINGS

Flammable, keep away from fire/flame,For external use only